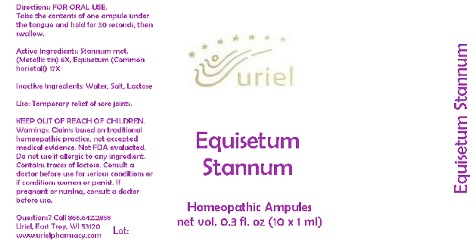 DRUG LABEL: Equisetum Stannum
NDC: 48951-4040 | Form: LIQUID
Manufacturer: Uriel Pharmacy Inc.
Category: homeopathic | Type: HUMAN OTC DRUG LABEL
Date: 20180517

ACTIVE INGREDIENTS: TIN 8 [hp_X]/1 mL; EQUISETUM ARVENSE TOP 17 [hp_X]/1 mL
INACTIVE INGREDIENTS: WATER; SODIUM CHLORIDE

Equisetum Stannum

INDICATIONS AND USAGE

Directions: FOR ORAL USE.

DOSAGE AND ADMINISTRATION

Take the contents of one ampule under the tongue and hold for 30 seconds, then swallow.

ACTIVE INGREDIENT

Active Ingredients: Stannum met. (Metallic tin) 8X, Equisetum (Common horsetail) 17X

Inactive Ingredients: Water, Salt, Lactose

PURPOSE

Use: Temporary relief of sore joints.

KEEP OUT OF REACH OF CHILDREN.

WARNINGS

Warnings: Claims based on traditional homeopathic practice, not accepted medical evidence. Not FDA evaluated. Do not use if allergic to any ingredient. Contains traces of lactose. Consult a doctor before use for serious conditions or if conditions worsen or persist. If pregnant or nursing, consult a doctor before use.

QUESTIONS

Questions? Call 866.642.2858 Uriel, East Troy, WI 53120 www.urielpharmacy.com